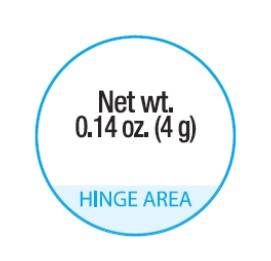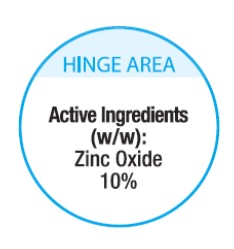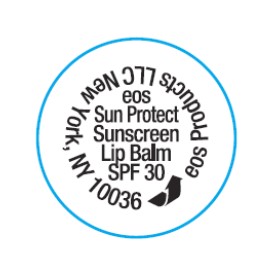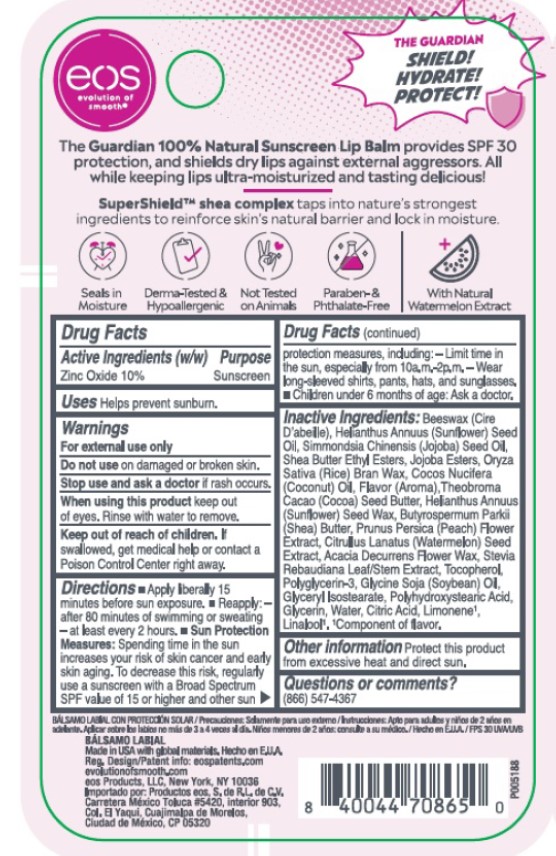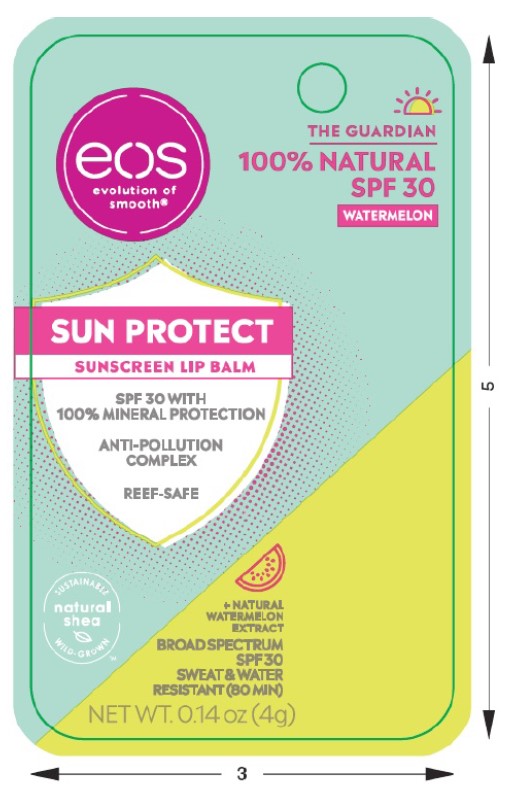 DRUG LABEL: eos THE GUARDIAN 100% NATURAL SPF 30 WATERMELON SUN PROTECT SUNSCREEN LIP BALM
NDC: 70170-0016 | Form: STICK
Manufacturer: eos Products LLC
Category: otc | Type: HUMAN OTC DRUG LABEL
Date: 20241030

ACTIVE INGREDIENTS: ZINC OXIDE 0.4 g/4 g
INACTIVE INGREDIENTS: SUNFLOWER OIL; YELLOW WAX; RICE BRAN; COCONUT OIL; SHEA BUTTER; COCOA BUTTER; JOJOBA OIL; HYDROLYZED JOJOBA ESTERS (ACID FORM); HELIANTHUS ANNUUS SEED WAX; PRUNUS PERSICA FLOWER; WATERMELON SEED; ACACIA DECURRENS FLOWER WAX; STEVIA REBAUDIUNA LEAF; TOCOPHEROL; POLYGLYCERIN-3; SOYBEAN OIL; GLYCERYL ISOSTEARATE; POLYHYDROXYSTEARIC ACID (2300 MW); GLYCERIN; WATER; CITRIC ACID MONOHYDRATE; LIMONENE, (+)-; LINALOOL, (+)-; SHEA BUTTER ETHYL ESTERS

eos THE GUARDIAN 100% NATURAL SPF 30 WATERMELON SUN PROTECT SUNSCREEN LIP BALM

Drug Facts

Active ingredients Purpose

Zinc Oxide 10% Sunscreen

Uses

Helps prevent sunburn.

Warnings

For external use only.

Do not useon damaged or broken skin.

Stop use and ask a doctor ifrash occurs.

WHEN USING

When using this productkeep out of eyes. Rinse with water to remove.

Keep out of reach of children.If swallowed, get medical help or contact a Poison Control Center right away.

Directions

- Apply liberally 15 minutes before sun exposure
- Reapply:

- after 80 minutes of swimming or sweating
- at least every 2 hours

- Sun Protection Measures: Spending time in the sun increases your risk of skin cancer and early skin aging. To decrease this risk, regularly use a sunscreen with a Broad Spectrum SPF value of 15 or higher and other sun protection measures, including:

- Limit time in the sun, especially from 10 a.m. - 2 p.m.

- Wear long-sleeved shirts, pants, hats, and sunglasses

- Children under 6 months of age: Ask a doctor.

Inactive ingredients

Beeswax (Cire D’abeille), Helianthus Annuus (Sunflower) Seed Oil, Simmondsia Chinensis (Jojoba) Seed Oil, Shea Butter Ethyl Esters, Jojoba Esters, Oryza Sativa (Rice) Bran Wax, Cocos Nucifera (Coconut) Oil, Flavor (Aroma), Theobroma Cacao (Cocoa) Seed Butter, Helianthus Annuus (Sunflower) Seed Wax, Butyrospermum Parkii (Shea) Butter, Prunus Persica (Peach) Flower Extract, Citrullus Lanatus (Watermelon) Seed Extract, Acacia Decurrens Flower Wax, Stevia Rebaudiana Leaf/Stem Extract, Tocopherol, Polyglycerin-3, Glycine Soja (Soybean) Oil, Glyceryl Isostearate, Polyhydroxystearic Acid, Glycerin, Water, Citric Acid, Limonene^1, Linalool^1.^1Component of flavor.

Other information

Protect this product from excessive heat and direct sun.

Questions or comments?

(866) 547-4367

Principal Display Panel - 0.14 oz (4 g)

eos

THE GUARDIAN

100% NATURAL

SPF 30

WATERMELON

SUN PROTECT

SUNSCREEN LIP BALM

SPF 30 WITH

100% MINERAL PROTECTION

ANTI-POLLUTION COMPLEX

REEF-SAFE

+NATURAL WATERMELON EXTRACT

BROAD SPECTRUM

SPF 30

SWEAT & WATER

RESISTANT (80 MIN)

NET WT. 0.14 oz (4g)